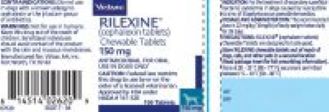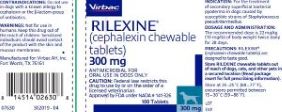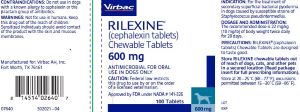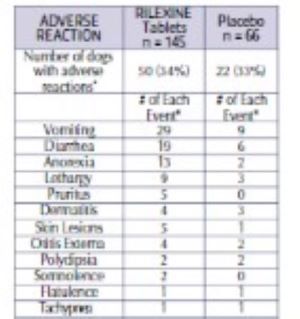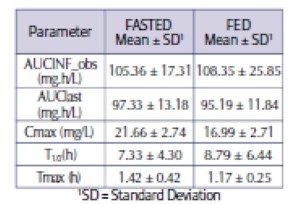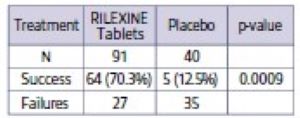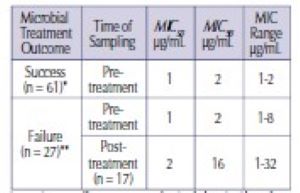 DRUG LABEL: RILEXINE
NDC: 51311-026 | Form: TABLET, CHEWABLE
Manufacturer: Virbac AH, Inc
Category: animal | Type: PRESCRIPTION ANIMAL DRUG LABEL
Date: 20240627

ACTIVE INGREDIENTS: CEPHALEXIN 150 mg/1 1

RILEXINE® (cephalexin tablets) Chewable Tablets

Antimicrobial for Oral Use in Dogs only

CAUTION

Federal law restricts this drug to use by or on the order of a licensed veterinarian.

DESCRIPTION

RILEXINE chewable tablets are a chewable, bisected tablet supplied in 3 sizes containing 150 mg, 300 mg, and 600 mg of cephalexin. Cephalexin is a cephalosporin, beta-lactam, broad spectrum antibiotic. The full chemical name for cephalexin is 7-(D-ɑ-amino-ɑ-phenylacetamido)-3-methyl-3-cephem-4-carboxylic acid monohydrate

INDICATION

For the treatment of secondary superficial bacterial pyoderma in dogs caused by susceptible strains of Staphylococcus pseudintermedius.

DOSAGE AND ADMINISTRATION

The recommended dose is 22 mg/kg (10 mg/lb) of body weight twice daily for 28 days.

Appropriate culture and susceptibility tests should be performed before treatment to determine the causative organism and its susceptibility to cephalexin. Therapy with RILEXINE chewable tablets may be initiated before results of these tests are known; once the results become available, antimicrobial therapy should be adjusted accordingly. If acceptable response to treatment is not observed, then the diagnosis should be re-evaluated and appropriate alternative therapy considered.

CONTRAINDICATIONS

RILEXINE chewable tablets are contraindicated in dogs with a known allergy to cephalexin or to the β-lactam (any of the penicillins or cephalosporins) group of antibiotics.

WARNINGS

For use in dogs only. Not for use in humans. Keep this drug out of the reach of children. Antimicrobials, including penicillins and cephalosporins, can cause allergic reactions in sensitized individuals. Sensitized individuals handling such antimicrobials, including cephalexin, should avoid contact of the product with the skin and mucous membranes in order to minimize the risk of allergic reactions.

In case of ingestion by humans contact a physician immediately. Physicians may contact a poison control center for advice concerning cases of ingestion by humans.

PRECAUTIONS

Prescribing antibacterial drugs in the absence of a proven or strongly suspected bacterial infection is unlikely to provide benefit to treated animals and may increase the risk of the development of drug-resistant animal pathogens.

RILEXINE chewable tablets are designed to taste good. Store RILEXINE chewable tablets out of reach of dogs, cats, and other pets in a secured location. Post approval experience has shown that dogs and cats may willingly consume more than the recommended dosage of RILEXINE chewable tablets, which can result in overdose. Adverse reactions may occur if large quantities of tablets are ingested (see Adverse Reactions, Animal Safety, and Information for Dog Owners sections). If the product is dispensed in a container other than the original, prescribers should consider adding a statement on the bottle label reminding the owner that RILEXINE chewable tablets are designed to taste good and should be stored out of reach of pets in a secured location.

The safe use of RILEXINE chewable tablets in dogs intended for breeding and in pregnant or lactating bitches has not been evaluated.

Positive direct Coombs’ test results and false positive reactions for glucose in the urine have been reported during treatment with some cephalosporin antimicrobials. Cephalosporin antimicrobials may also cause falsely elevated urine protein determinations. Some antimicrobials, including cephalosporins, can cause lowered albumin values due to interference with certain testing methods.

Occasionally, cephalosporins have been associated with myelotoxicity, thereby creating a toxic neutropenia.1 Other hematological reactions observed with cephalosporin therapy include neutropenia, anemia, hypoprothrombinemia, thrombocytopenia, prolonged prothrombin time (PT) and partial thromboplastin time (PTT), platelet dysfunction, and transient increases in serum aminotransferases.2

ADVERSE REACTIONS

The most common adverse reactions in dogs include diarrhea, vomiting, anorexia and lethargy.

A total of 211 dogs were included in the field study safety analysis. Adverse reactions reported in dogs treated with RILEXINE chewable tablets and placebo are summarized in Table 1.

Table 1: Number of Adverse Reactions* Reported During the Field Study with RILEXINE Chewable Tablets

*Some dogs may have experienced more than one adverse reaction or more than one occurrence of the same adverse reaction during the study.

No clinically significant differences were observed in the mean values for all laboratory tests including urinalysis between RILEXINE Chewable Tablets and placebo-treated dogs. At the end of treatment, group means for neutrophils, WBC, and globulin values were significantly higher in the placebo group than in the RILEXINE Chewable Tablets group; whereas, group mean values for eosinophils, A/G Ratio values, and total protein values were significantly higher in the RILEXINE Chewable Tablets group than in the placebo group. For all six of these parameters, the differences were not clinically significant and the mean values for each of the parameters remained within the normal range.

To report suspected adverse drug events and/or obtain a copy of the Safety Data Sheet (SDS) or for technical assistance, contact Virbac at 1-800-338-3659. For additional information about adverse drug experience reporting for animal drugs, contact FDA at 1-888-FDAVETS or online at http://www.fda.gov/AnimalVeterinary/SafetyHealth

INFORMATION FOR DOG OWNERS: Owners should be advised that RILEXINE Chewable Tablets are designed to taste good. Owners should be instructed to keep the product in a secured storage area out of the reach of pets in order to prevent accidental ingestion or overdose. Post approval experience has shown that dogs and cats may willingly consume more than the recommended dosage of RILEXINE Chewable Tablets. Adverse reactions may occur if large quantities of tablets are ingested (see Precautions, Adverse Reactions, and Animal Safety sections).

Owners should be advised to contact their veterinarian immediately and notify Virbac (1-800-338-3659) if the dog ingests more tablets than prescribed or if other pets ingest RILEXINE Chewable Tablets. In the case of accidental ingestion by humans, contact a physician immediately.

CLINICAL PHARMACOLOGY

Cephalexin belongs to the cephalosporin family of bactericidal antibiotics.

Cephalexin is readily and almost completely absorbed following oral administration (90% absolute bioavailability). Blood concentrations are proportional to dose within the range of at least 15 to 45 mg/kg. Binding to canine plasma proteins is low, ranging from 9 to 13% for cephalexin concentrations of 0.5 to 100 g/mL.

Food reduces the peak cephalexin concentrations but has negligible effect on the extent of absorption.

A summary of the pharmacokinetics (PK) observed in fed and fasted Beagle dogs administered a single 22 mg/kg dose is provided in Table 2.

Table 2: Pharmacokinetics Parameter values (mean ± standard deviation), protein-corrected in fasted and fed dogs following a single administration of 22 mg/kg dose of RILEXINE chewable tablets (N = 12)

Cephalosporins are associated with time dependent killing effects. Accordingly, the pharmacodynamic (PD) target is time above MIC (T>MIC). For

staphylococcal infections, the goal for time above MIC is 40% of the dosing interval (which translates to 4.8 hrs for a BID dosing schedule). For streptococcal infections, the target for time above MIC is 60% of the dosing interval (i.e., 7.2 hrs). To assess whether or not the PK-PD target is met with a 22 mg/kg BID dosing regimen under fed and fasted conditions, it was assumed that the MIC90 for S.pseudintermedius is 2 μg/mL. Plasma drug concentrations were normalized to exactly 22 mg/kg dose and corrected for 10% protein binding (protein binding observed in canine plasma).

Under fasted conditions, all targets were met in all dogs after the first daily dose. With food, the target for S. aureus was met by the second daily dose. Therefore, a 22 mg/kg BID dosing interval under fed or fasted conditions succeeded in attaining the PK-PD targets.

MICROBIOLOGY

Cephalexin is a cephalosporin antibiotic. Like other -lactam antimicrobials, cephalexin exerts its inhibitory effect by interfering with bacterial cell wall synthesis. This interference is primarily due to its covalent binding to the penicillin-binding proteins (PBPs) (i.e., transpeptidase and carboxypeptidase), which are essential for synthesis of the bacterial wall. Minimum Inhibitory Concentrations (MICs) for cephalexin against label-claim pathogens isolated from canine pyoderma in a 2008-2009 U.S. field trial are presented in Table 3. All MICs were determined in accordance with the Clinical Laboratory Standards Institute (CLSI) standards.

Table 3: Summary of Cephalexin MIC values against S. pseudintermedius isolates from 88 dogs treated with RILEXINE® (cephalexin tablets) Chewable Tablets for bacterial pyoderma in a U.S. field study during 2008-2009

*No post-treatment sampling was conducted due to the absence of lesions.

**Of the 27 failures, 10 did not have positive post-treatment cultures.

EFFECTIVENESS

The clinical effectiveness of RILEXINE Chewable Tablets was established in a randomized, multi-location, placebocontrolled field study (see Table 4). In this study, 131 dogs with secondary superficial bacterial pyoderma treated with either RILEXINE Chewable Tablets (n = 91) at 22 mg/kg (10 mg/lb) body weight or with a negative control (n = 40), twice daily for 28 days, were analyzed. RILEXINE Chewable Tablets were considered superior to the placebo (70% success rate vs. 13% respectively) in the treatment of secondary superficial bacterial pyoderma caused by susceptible strains of S. pseudintermedius.

Table 4: Primary endpoint: Percentage of Cure* in the Effectiveness population

*Absence of lesions at the end of the study.

PALATABILITY: The palatability of RILEXINE chewable tablets was evaluated in two separate multi-location studies. In the first study, 39
client-owned dogs were dosed with RILEXINE chewable tablets at 22mg/kg and evaluated for palatability of the product. Palatability testing was
performed twice daily prior to feeding for 7 days. Dogs freely consumed (from empty bowl or open hand) 80.8% of their doses. In a second study, 64 client-owned dogs enrolled in the field efficacy study were evaluated in a similar manner and freely consumed 78.4% of their doses.

ANIMAL SAFETY

RILEXINE chewable tablets were administered orally three times a day to 12-week-old healthy Beagles at 0mg/kg (placebo), 22mg/kg (1X), 66mg/kg (3X), and 110 mg/kg (5X) for 12 weeks, and at 22 mg/kg twice a day for 12 weeks. The most common clinical findings included
epiphora, salivation, vomiting and diarrhea among all the dose groups. Three dogs had decreased activity (1 in each from the 22 mg/kg twice a day, 22 mg/kg three times a day, and the 66 mg/kg three times a day groups). These observations were mild and sporadic.

There were increases in alanine aminotransferase (ALT) in the 110 mg/kg three times a day group and in the 22 mg/kg twice a day group that increased in a dose-dependent pattern. There was an increase in sorbitol dehydrogenase (SDH) in the 110 mg/kg three times a day group compared to the controls. These changes were minimal and the values remained within expected historical control ranges. There were several decreases in total protein (in the 110 mg/kg three times a day group) and/or globulin (in the 22, 66, and 110 mg/kg three times a day groups) compared to the controls. These changes resulted in occasional increases in albumin/globulin ratios. Although a drug effect cannot be ruled out, these changes were not clinically relevant.

A mild prolongation in prothrombin time (PT) was observed in the 22 mg/kg three times a day group. This was not considered clinically relevant due to the small change that remained within the reference ranges.

One dog in the 110 mg/kg three times a day group had moderate amounts of bilirubinuria at the Week 8 and Week 12 samplings. No clinical significance was noted.

Cephalexin was not present in any Day 1 samples prior to dosing or in any control animals. After dosing, cephalexin was well absorbed into systemic circulation of the treated dogs. Within gender and dosage level, Week 8 mean trough concentrations were generally higher than the Week 4 and 12 mean trough concentrations (between a 0.9 and 3.6-fold difference). The geometric mean plasma cephalexin trough concentration following three times daily administration of the 110 mg/kg dose was 11.2 μg/mL compared to 2.6 μg/mL and 8.7 μg/mL following 22 mg/kg and 66 mg/kg, respectively at Week 12. Geometric mean plasma cephalexin trough concentrations following administration of 22 mg/kg twice daily were 0.7, 1.3, and 1.0 μg/mL at Weeks 4, 8, and 12, respectively.

STORAGE IN FORMATION

Store at 20 - 25°C (68 - 77°F), with excursions permitted between 15 - 30°C (59 - 86°F).

HOW SUPPLIED

RILEXINE® (cephalexin tablets) Chewable Tablets are supplied in 150 mg, 300 mg, and 600 mg tablets packaged in bottles of 100 tablets.

Approved by FDA under NADA # 141-326

Manufactured for: Virbac AH, Inc.
Fort Worth, TX 76161 USA

150 mg 07620 302054 - 05, 300 mg 07630 302055-05 , 600 mg 07640 302056-05

Revision date: 01/2024

^1Birchard SJ and Sherding RG. Saunders Manual of Small Animal Practice, 2nd edition. W.B. Saunders Co. 2000: p. 166.
^2Adams HR. Veterinary Pharmacology and Therapeutics, 8th edition, 2001, p. 825.

© 2024 Virbac Corporation. All rights reserved. RILEXINE is a registered trademark of the Virbac Group of Companies.